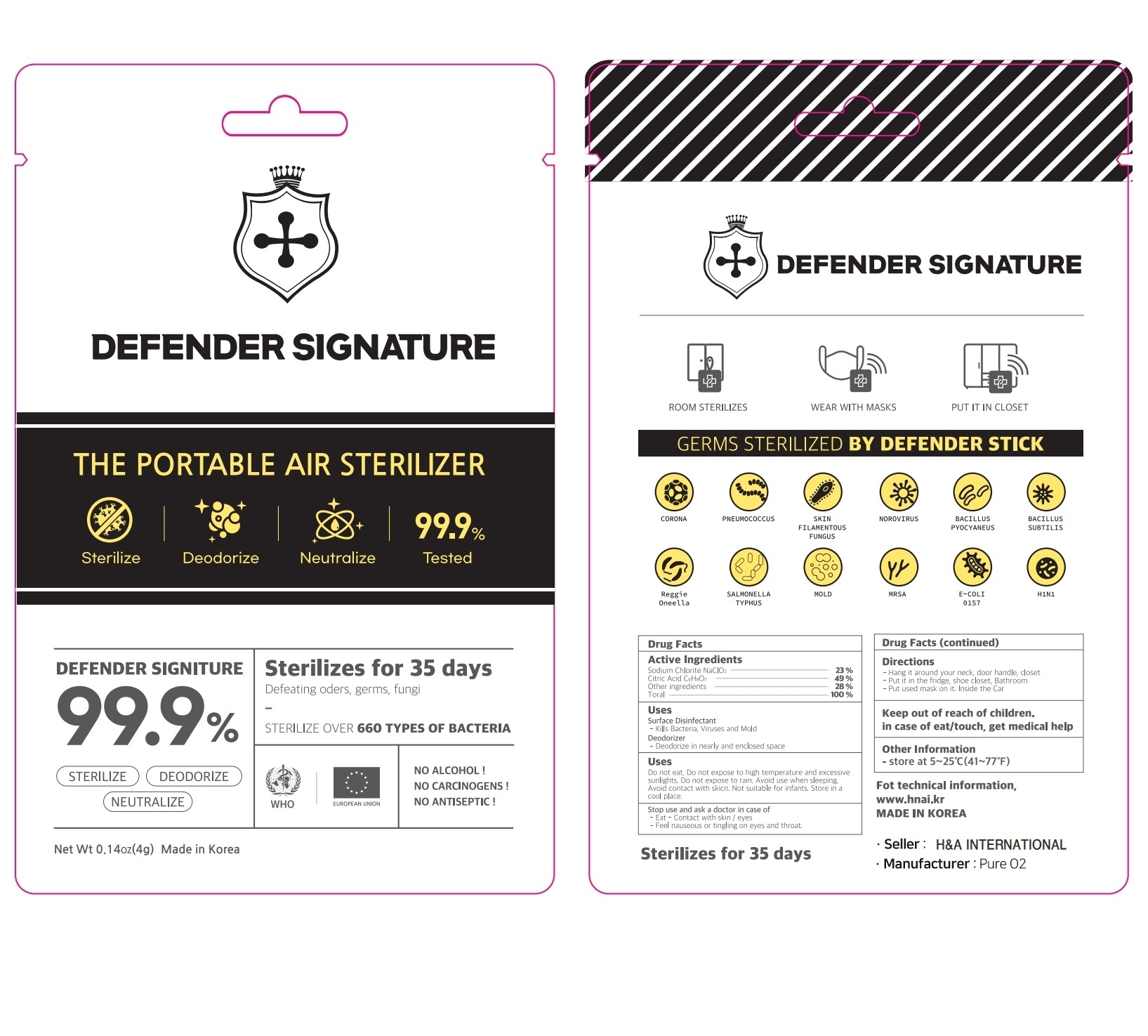 DRUG LABEL: DEFENDER SIGNATURE
NDC: 75124-0012 | Form: POWDER
Manufacturer: Pure O2
Category: otc | Type: HUMAN OTC DRUG LABEL
Date: 20210417

ACTIVE INGREDIENTS: SODIUM CHLORITE 23 g/100 g
INACTIVE INGREDIENTS: CITRIC ACID MONOHYDRATE; SODIUM BISULFATE

Drug Facts

ACTIVE INGREDIENT

sodium chlorite

INACTIVE INGREDIENT

citric acid, sodium bisulfate

PURPOSE

anti bacteria, virus, odors

KEEP OUT OF REACH OF THE CHILDREN

INDICATIONS AND USAGE

kills bacteria, viruses and molds

WARNINGS

■ For external use only.

■ Do not use in eyes.

■ lf swallowed, get medical help promptly.

■ Stop use, ask doctor lf irritation occurs.

■ Keep out of reach of children.

DOSAGE AND ADMINISTRATION

for external use only